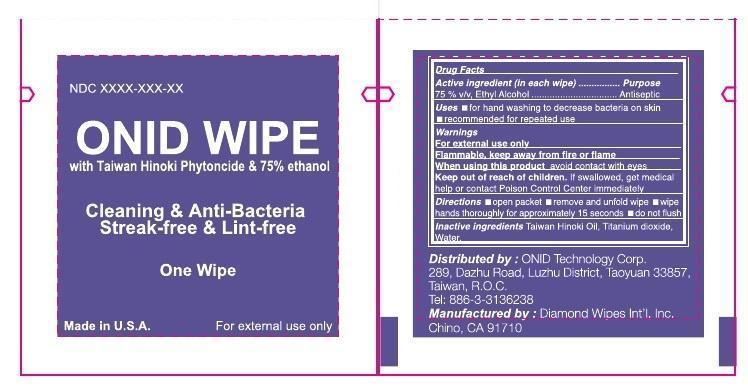 DRUG LABEL: ONID Wipe
NDC: 71441-180 | Form: SWAB
Manufacturer: ONID Technology Corp
Category: otc | Type: HUMAN OTC DRUG LABEL
Date: 20170628

ACTIVE INGREDIENTS: ALCOHOL 75 mL/100 mL
INACTIVE INGREDIENTS: Water 24.9 mL/100 mL; TITANIUM DIOXIDE 1 mL/100 mL; CHAMAECYPARIS OBTUSA WOOD OIL .1 mL/100 mL

Active Ingredient

Ethyl Alcohol 75%

Purpose

Antiseptic

Uses

- For hand washing to decrease bacteria on the skin
- Reccomended for repeated use

Directions

- open packet
- remove and unfold wipe
- wipe hands throughly for approximately 15 seconds
- do not flush

Keep Out of Reach of Children

If swollowed get medical help or contact Poision Control Center imediately.

Inactive Ingredients

Taiwan Hinoki oil, titanium dioxide, water